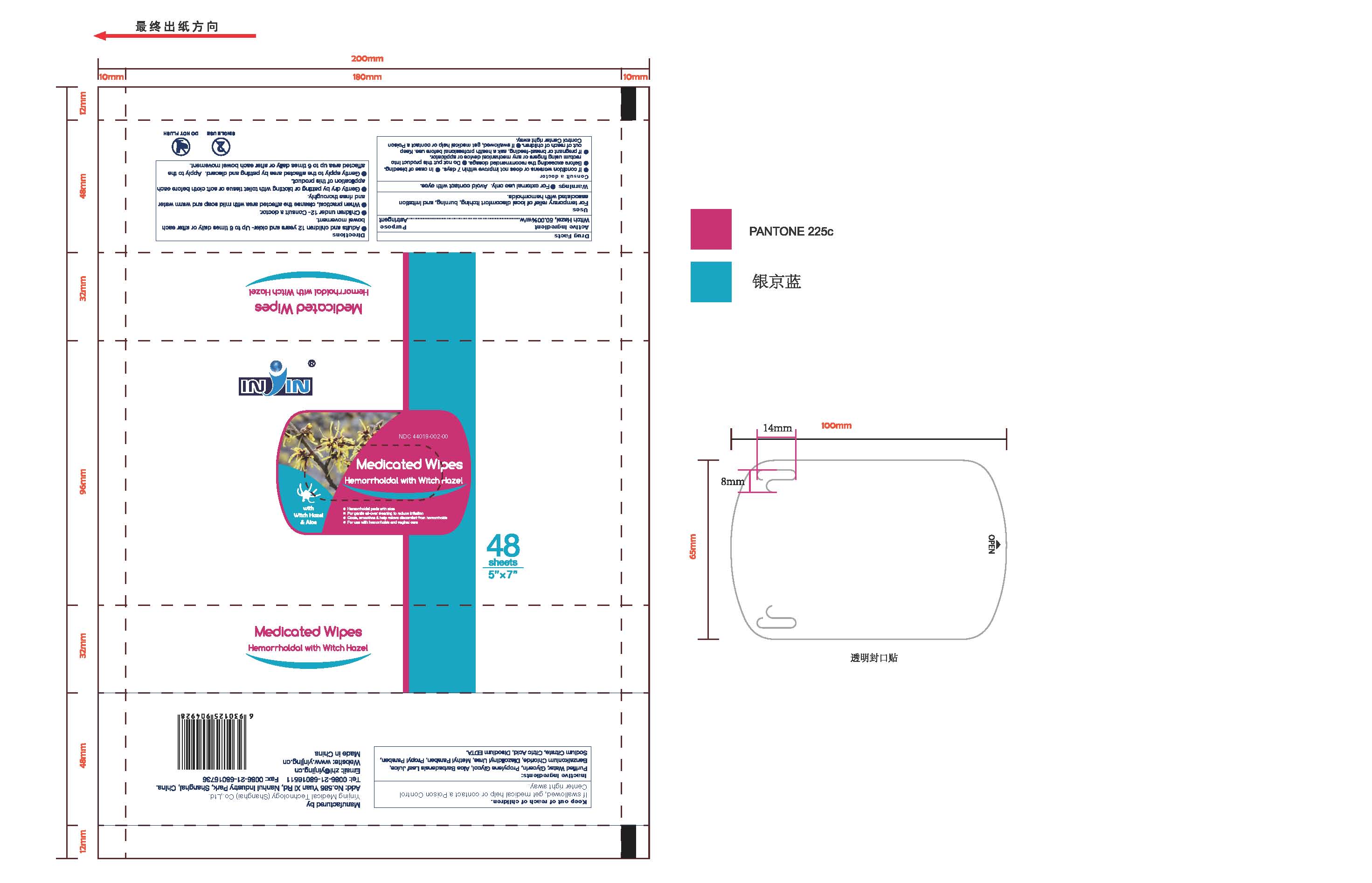 DRUG LABEL: Flushable Medicated Wipes Hemorrhoidal Pads with Witch Hazel and Aloe
NDC: 44019-002 | Form: LIQUID
Manufacturer: Yinjing Medical Technology (Shanghai) Co., Ltd.
Category: otc | Type: HUMAN OTC DRUG LABEL
Date: 20171227

ACTIVE INGREDIENTS: WITCH HAZEL 50 g/100 g
INACTIVE INGREDIENTS: WATER; GLYCERIN; PROPYLENE GLYCOL; ALOE VERA LEAF; BENZALKONIUM CHLORIDE; DIAZOLIDINYL UREA; METHYLPARABEN; PROPYLPARABEN; SODIUM CITRATE; CITRIC ACID MONOHYDRATE; EDETATE DISODIUM

Flushable Medicated Wipes Hemorrhoidal Pads with Witch Hazel and Aloe

Active ingredient

Witch Hazel,50% v/v

Purpose

Astringent

Uses

For temporary relief of local discomfort itching, burning, and irritation associated with hermorrhoids.

Warnings

For external use only. Avoid contact with eyes.

Consult a doctor

- If condition worsens or does not improve within 7 days.
- In case of bleeding.
- Before exceeding the recommended dosage.
- Do not put this product into rectum using fingers or any mechanical device or applicator.
- If pregnant or breast-feeding, ask a health professional before use.

Keep out of reach of children.

?If swallowed, get medical help or contact a Poison Control Center right away.

Directions

- Adults and children 12 years and older- Up to 6 times daily or after each bowel movement ? Children under 12- Consult a doctor ? When practical, cleanse the affected area with mild soap and warm water and rinse thoroughly. ? Gently dry by patting or blotting with toilet tissue or soft cloth before each application of this product. ? Gently apply to the affected area by patting and discard. Apply to the affected area up to 6 times daily or after each bowel movement

Other information

Store at room temperature 15^0 - 30^0 C (59^0 - 86^0 F)

Inactive Ingredient

Purified Water, Glycerin, Propylene Glycol, Aloe Barbadensis Leaf Juice, Benzalkonium Chloride, Diazolidinyl Urea, Methyl Paraben, Propyl Paraben, Sodium Citrate, Citric Acid, Disodium EDTA.

PACKAGE LABEL

IN IN NDC:

Flushable Medicated Wipes 48 Medicated Wipes 5in*6in (12.7cmx15.2cm) Hemorrhoidal pads with Witch Hazel and Aloe For gental every cleaning to reduce irritation Cools, smoothes and Help Relieve Discomfort from Hemorrhoids For use with Hemorrhoids and Vaginal care convenient and Easy Use.